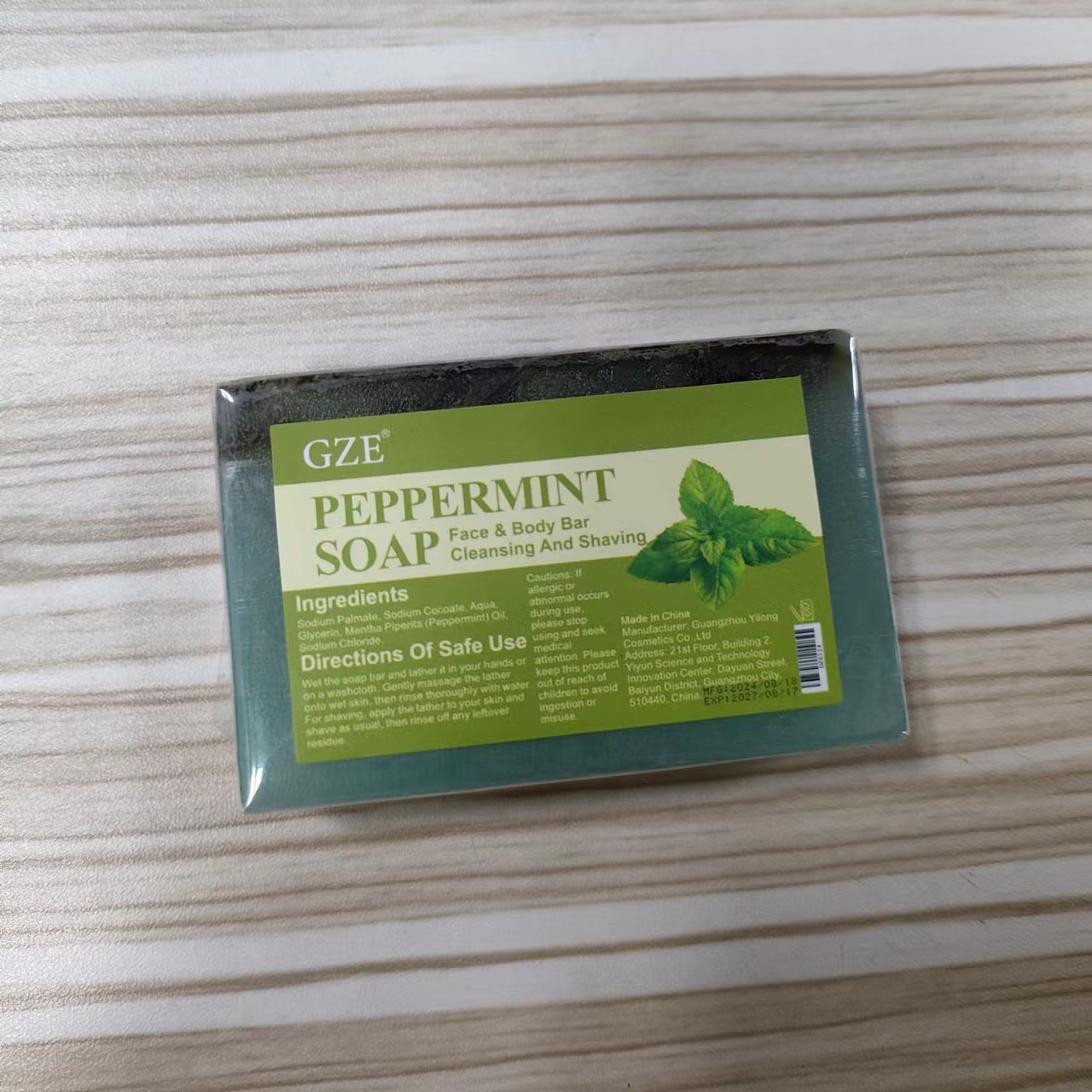 DRUG LABEL: GZE PeppermintSoap
NDC: 74458-328 | Form: SOAP
Manufacturer: Guangzhou Yilong Cosmetics Co., Ltd
Category: otc | Type: HUMAN OTC DRUG LABEL
Date: 20241108

ACTIVE INGREDIENTS: PEPPERMINT OIL 5 g/100 g
INACTIVE INGREDIENTS: SODIUM COCOATE; AQUA; GLYCERIN; SODIUM PALMATE

GZE PEPPERMINT SOAP

INACTIVE INGREDIENT

Sodium Palmate

Sodium Cocoate

Aqua

Glycerin

Sodium Chloride

ACTIVE INGREDIENT

Mentha Piperita (Peppermint) Oil

INDICATIONS AND USAGE

Wet the soap bar and lather it in your hands or on a washcloth. Gently massage the lather onto wet skin, then rinse thoroughly with water. For shaving, apply the lather to your skin and shave as usual, then rinse off any leftover residue.

PURPOSE

Clean skin.

WARNINGS

For external use only.

Stop use and ask a doctor if rash occurs.

Do not use on damaged or broken skin.

When using this product keep out of eyes. Rinse with water to remove.

Keep out of reach of children. If swallowed, get medical help or contact a Poison Control Center right away.

DOSAGE AND ADMINISTRATION

Wet the soap bar and lather it in your hands or on a washcloth. Gently massage the lather onto wet skin, then rinse thoroughly with water. For shaving, apply the lather to your skin and shave as usual, then rinse off any leftover residue.